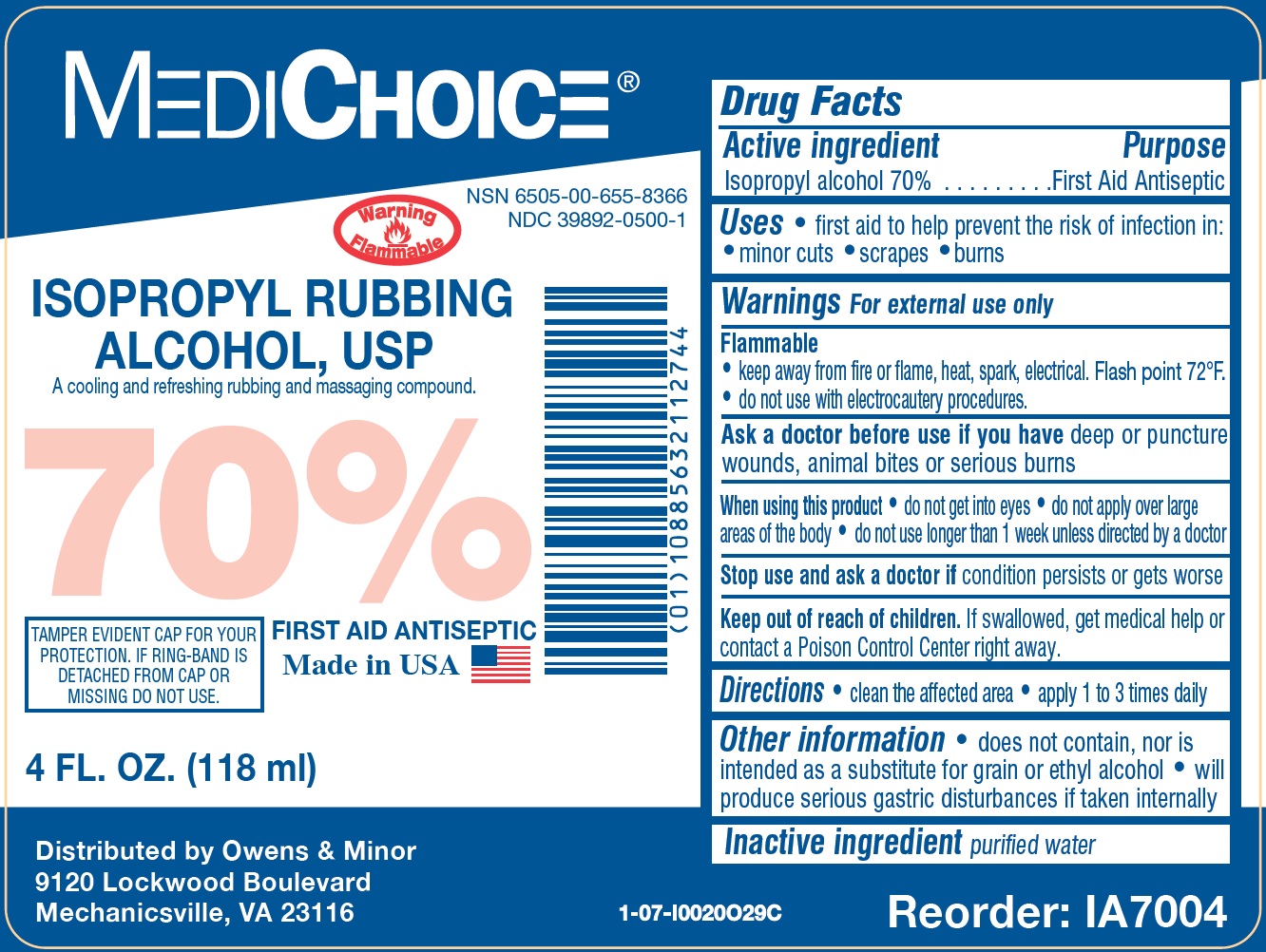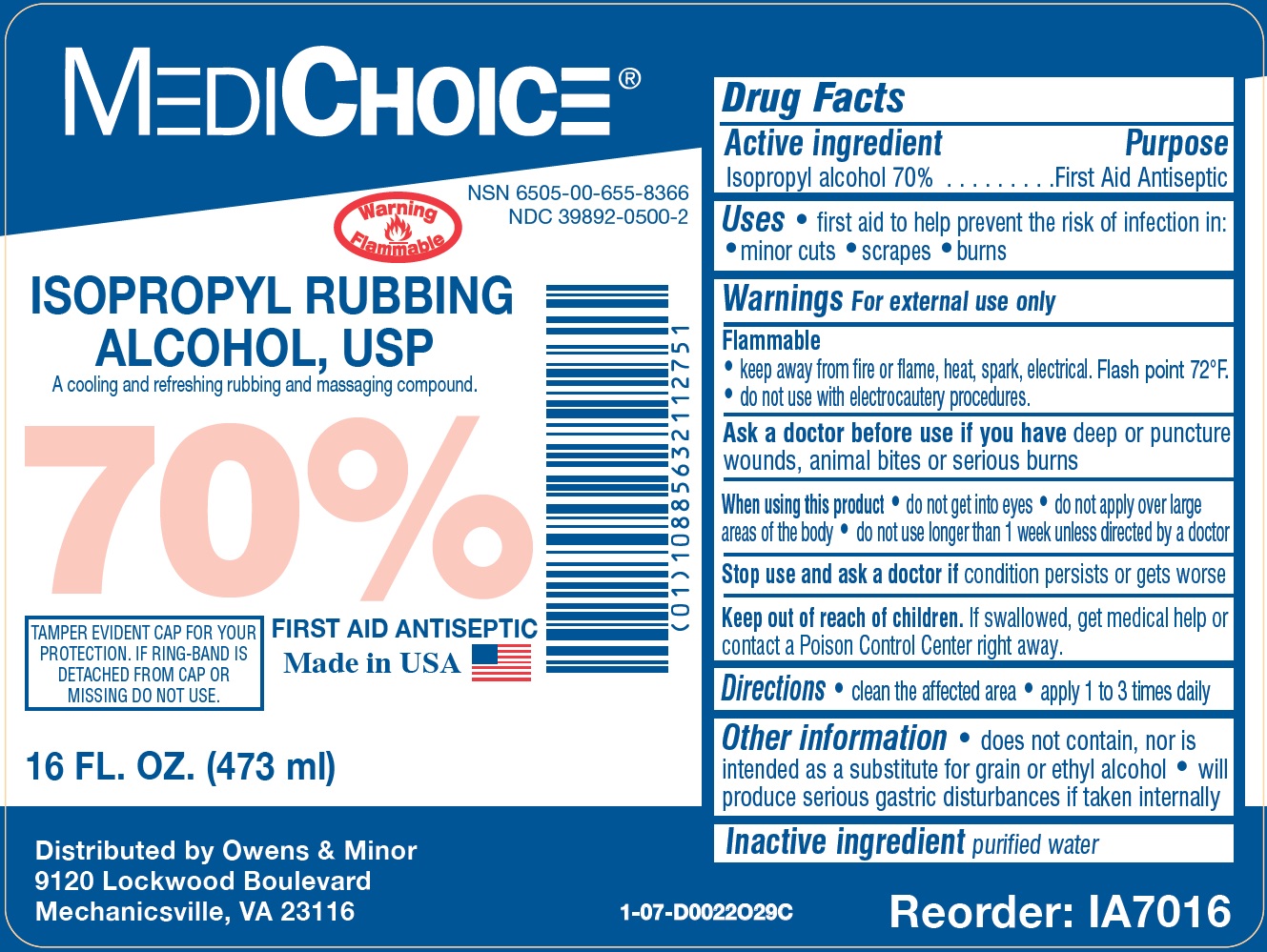 DRUG LABEL: MediChoice Isopropyl Rubbing Alcohol
NDC: 39892-0500 | Form: LIQUID
Manufacturer: O&M HALYARD, INC.
Category: otc | Type: HUMAN OTC DRUG LABEL
Date: 20251008

ACTIVE INGREDIENTS: ISOPROPYL ALCOHOL 700 mg/1 mL
INACTIVE INGREDIENTS: WATER

MediChoice Isopropyl Rubbing Alcohol

Active ingredient

Isopropyl alcohol 70%

Purpose

First Aid Antiseptic

Uses

• first aid to help prevent the risk of infection in: • minor cuts • scrapes • burns

Warnings

For external use only

• keep away from fire or flame, heat, spark, electrical. Flash point 72°F. • do not use with electrocautery procedures. Flammable

Ask a doctor before use if you have

deep or puncture wounds, animal bites or serious burns

When using this product

• do not get into eyes • do not apply over large areas of the body • do not use longer than 1 week unless directed by a doctor

Stop use and ask a doctor if

condition persists or gets worse

Keep out of reach of children.

If swallowed, get medical help or contact a Poison Control Center right away.

Directions

• clean the affected area • apply 1 to 3 times daily

Other information

• does not contain, nor is intended as a substitute for grain or ethyl alcohol • will produce serious gastric disturbances if taken internally

Inactive ingredient

purified water